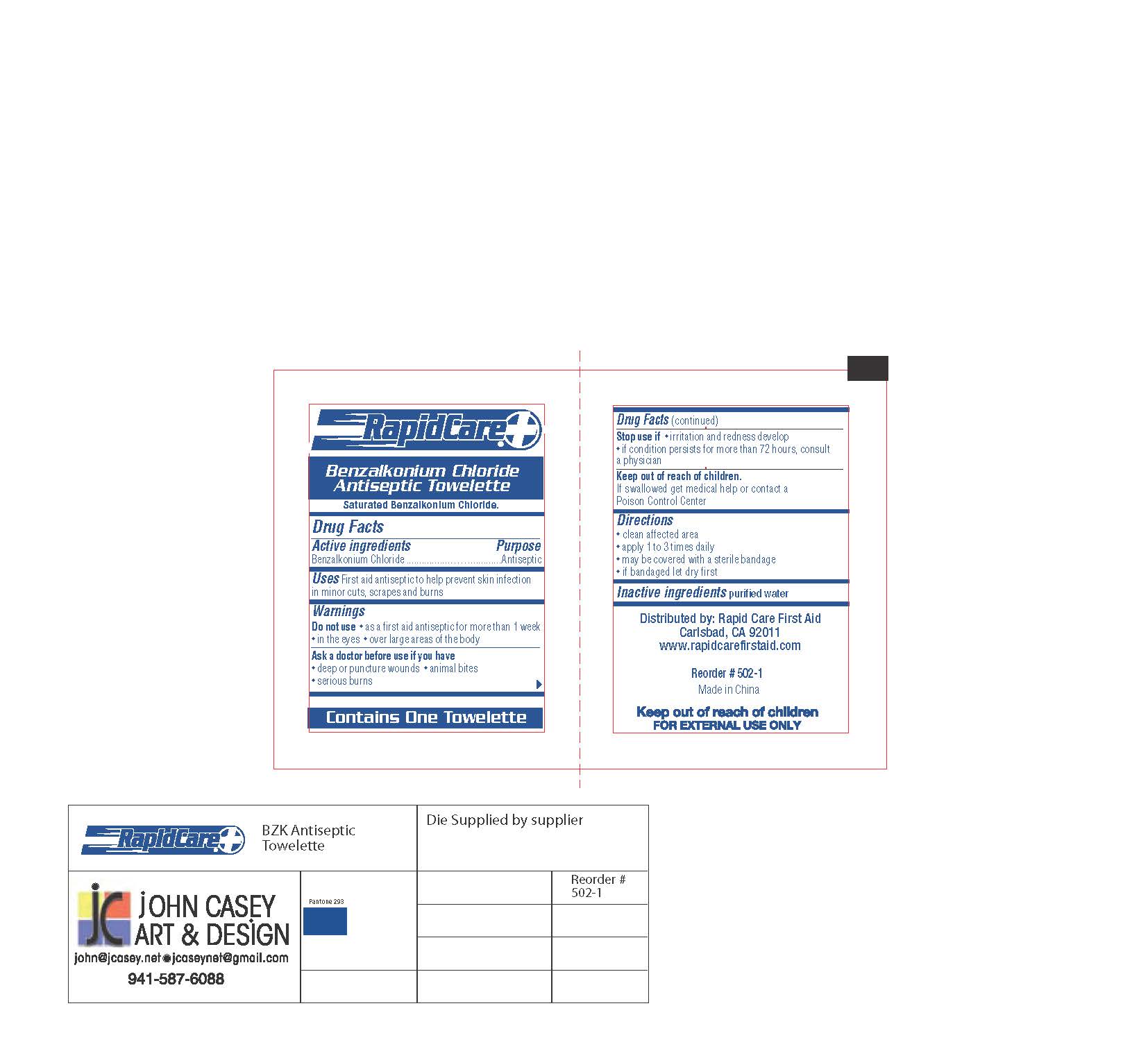 DRUG LABEL: Benzalkonium Chloride Antiseptic Towelette
NDC: 73659-003 | Form: SWAB
Manufacturer: Rapid Care, Inc
Category: otc | Type: HUMAN OTC DRUG LABEL
Date: 20211014

ACTIVE INGREDIENTS: BENZALKONIUM CHLORIDE 0.13 g/1 1
INACTIVE INGREDIENTS: WATER

RapidCare - Benzalkonium Chloride Antiseptic Towelette - 1pc

Active Ingredients

Benzalkonium Chloride

Purpose

Antiseptic

Use

First aid antiseptic to help prevent skin infection in minor cuts, scrapes and burns

Warnings

For external use only

Do Not Use

- as a first aid antiseptic for more than 1 week
- in the eyes
- over large areas of the body

Ask a doctor before use if you have

- deep or puncture wounds
- animal bites
- serious burns

Stop use if

- irritation and redness develop
- if condition persists for more than 72 hours, consult a physician

Keep out of reach of children.

If swallowed get medical help or contact a Poison Control right away.

Directions

- clean affected area
- apply 1 to 3 times daily
- may be covered with a sterile bandage
- if bandaged let dry first

Other Information

stor at room temperaturel15°-30° C (59°-86° F)

Inactive ingredient

purified water